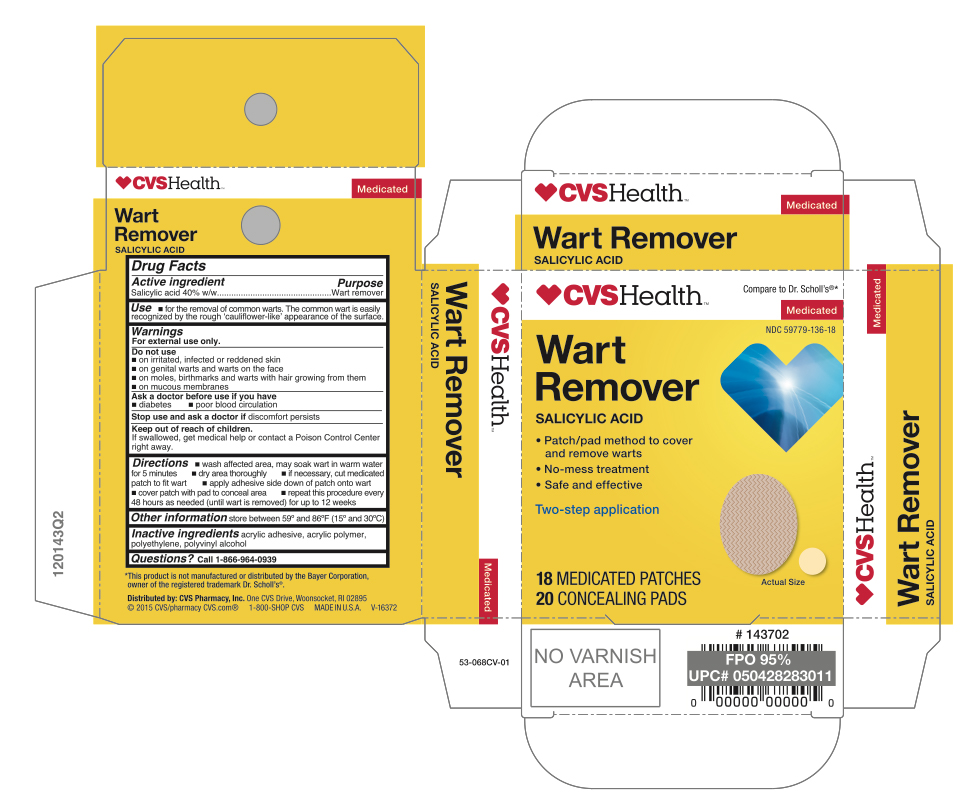 DRUG LABEL: Salicylic Acid
NDC: 59779-136 | Form: PATCH
Manufacturer: CVS Pharmacy
Category: otc | Type: HUMAN OTC DRUG LABEL
Date: 20241115

ACTIVE INGREDIENTS: SALICYLIC ACID 40 mg/18 1
INACTIVE INGREDIENTS: VINYL ACETATE; HIGH DENSITY POLYETHYLENE; POLYVINYL ALCOHOL

CVS Wart Remover

Active ingredient

Salicylic acid 40w/w%

Purpose

Wart remover

Use

For the removal of common warts. The common wart has a rough 'cauliflower-like' appearance.

Warnings

For external use only.

Do not use

- if you are a diabetic or have poor blood circulation, except under the advice and supervision of a doctor or podiatrist
- on irritated, infected or reddened skin
- on genital warts and warts on the face
- on moles, birthmarks and warts with hair growing from them
- on mucous membranes

Keep out of reach of children

If swallowed, get medical help or contact a Poison Control Center right away.

Stop and ask a doctor

If discomfort persists see your doctor or podiatrist

Directions

- wash affected area, may soak wart in warm water for 5 minutes
- dry area thoroughly
- if necessary, cut medicated patch to fit wart
- apply adhesive side down of patch onto wart
- cover patch with pad to conceal area
- repeat this procedure every 48 hours as needed (until wart is removed) for up to 12 weeks

Other information

store between 59°F to 86°F (15°C to 30°C)

Inactive ingredients

acrylic adhesive, acrylic polymer, polyvinyl alcohol, polyethylene

Questions?

Call 1-866-964-0939

Principal Display Panel

CVS Pharmacy

Wart Removers
Medicated Discs
Salicylic Acid

Patch/pad method to cover and remove warts
No mess treatment
Safe and effective
Two- Step application

18 Medicated Patches
20 Concealing Pads